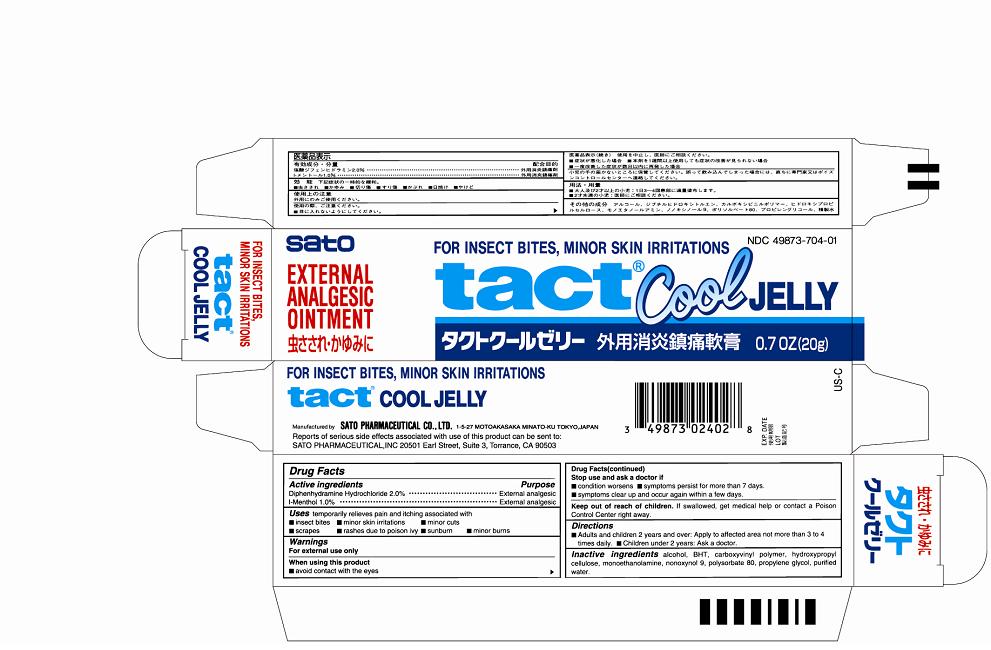 DRUG LABEL: Tact Cool
NDC: 49873-704 | Form: GEL
Manufacturer: Sato Pharmaceutical Co., Ltd.
Category: otc | Type: HUMAN OTC DRUG LABEL
Date: 20231201

ACTIVE INGREDIENTS: DIPHENHYDRAMINE HYDROCHLORIDE 2 g/100 g; LEVOMENTHOL 1 g/100 g
INACTIVE INGREDIENTS: ALCOHOL; BUTYLATED HYDROXYTOLUENE; CARBOMER HOMOPOLYMER TYPE C; HYDROXYPROPYL CELLULOSE; MONOETHANOLAMINE; NONOXYNOL-9; POLYSORBATE 80; PROPYLENE GLYCOL; WATER

Tact Cool Jelly

Active ingredients

Diphenhydramine Hydrochloride 2.0%
l-Menthol 1.0%

Uses

temporarily relieves pain and itching associated with
■insect bites ■minor skin irritations ■minor cuts
■scrapes ■rashes due to poison ivy ■sunburn ■minor burns

Warnings
For external use only

When using this product
■avoid contact with the eyes

Stop use and ask a doctor if
■condition worsens ■symptoms persist for more than 7 days.
■symptoms clear up and occur again within a few days.

Keep out of reach of children. If swallowed, get medical help or contact a Poison Control Center right away.

Directions
■Adults and children 2 years and over: Apply to affected area not more than 3 to 4 times daily. ■Children under 2 years: Ask a doctor.

INACTIVE INGREDIENT

I nactive ingredients alcohol, BHT, carboxyvinyl polymer, hydroxypropyl cellulose, monoethanolamine, nonoxynol 9, polysorbate 80, propylene glycol, purified water.

PURPOSE

Diphenhydramine Hydrochloride External analgesic
l-Menthol External analgesic

PACKAGE LABEL

tactcjcart.jpg